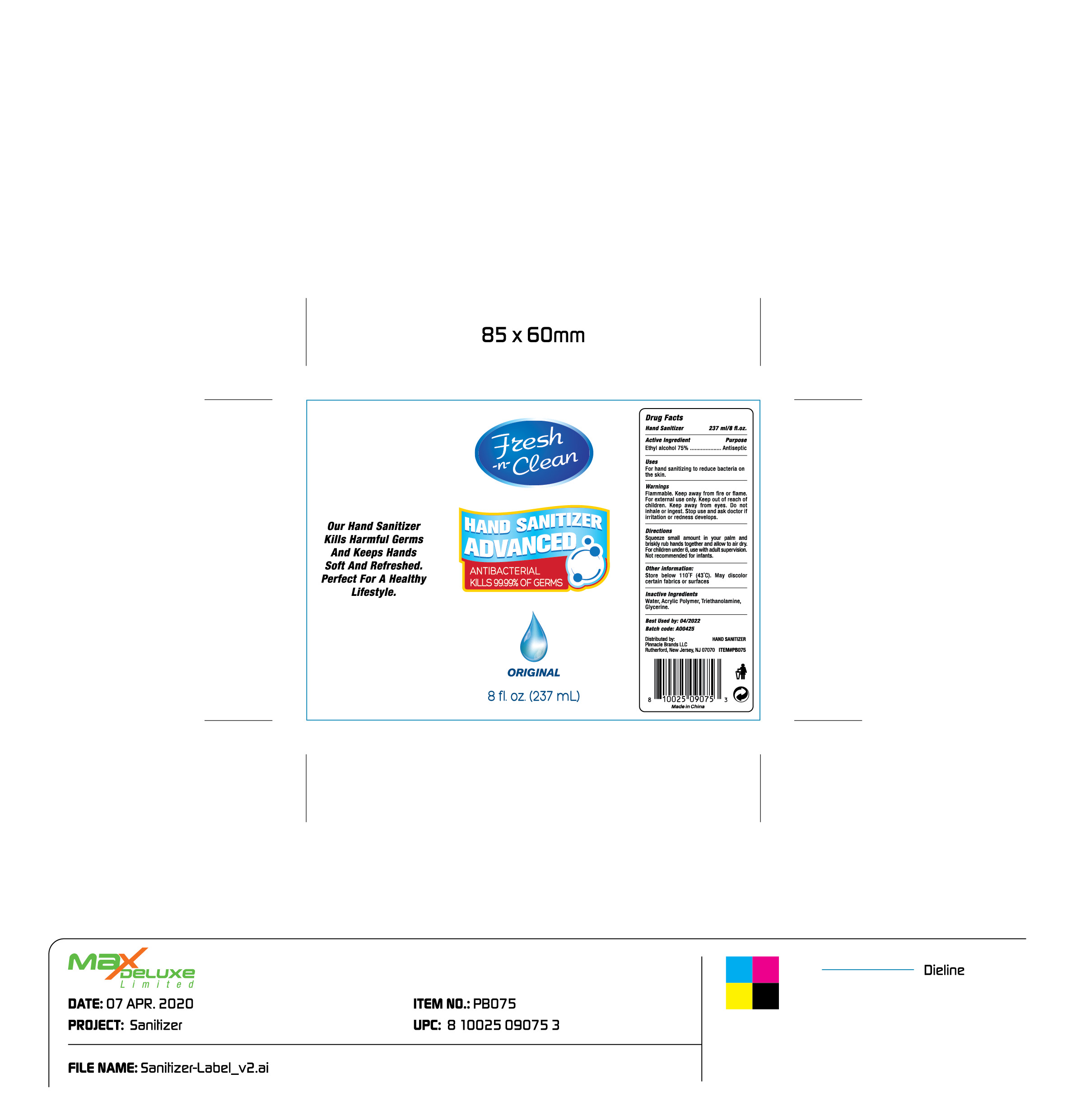 DRUG LABEL: 75% alcohol hand sanitizer
NDC: 75690-001 | Form: GEL
Manufacturer: Pinnacle Brands LLC
Category: otc | Type: HUMAN OTC DRUG LABEL
Date: 20230213

ACTIVE INGREDIENTS: ALCOHOL 75 mL/100 mL
INACTIVE INGREDIENTS: GLYCERIN; CARBOMER 940; WATER; TROLAMINE

75% alcohol hand sanitizer

ACTIVE INGREDIENT

Alcohol 75% v/v. Purpose: Antiseptic

PURPOSE

Antiseptic, Hand Sanitizer

INDICATIONS AND USAGE

For hand sannitizing to reduce bacteria on the skin.

WARNINGS

Flammable. Keep away from fire or flame. For external use only.

WHEN USING

Keep away from eyes.

Keep our of reach of children.

Do not inhale or ingest.

Stop use and ask doctor if irritation or redness develops.

DOSAGE AND ADMINISTRATION

Squeeze small amount in your palm and briskly rub hands together and allow to air dry.

For children under 6, use with adult supervision.

Not recommended for infants.

OTHER SAFETY INFORMATION

Store below 105F (43C). May discolor certain fabrics or surfaces.

INACTIVE INGREDIENT

Water, Acrylic Polymer, Triethanolamine, Glycerine.

Package Label - Principal Display Panel

237 mL NDC: 74621-001-04